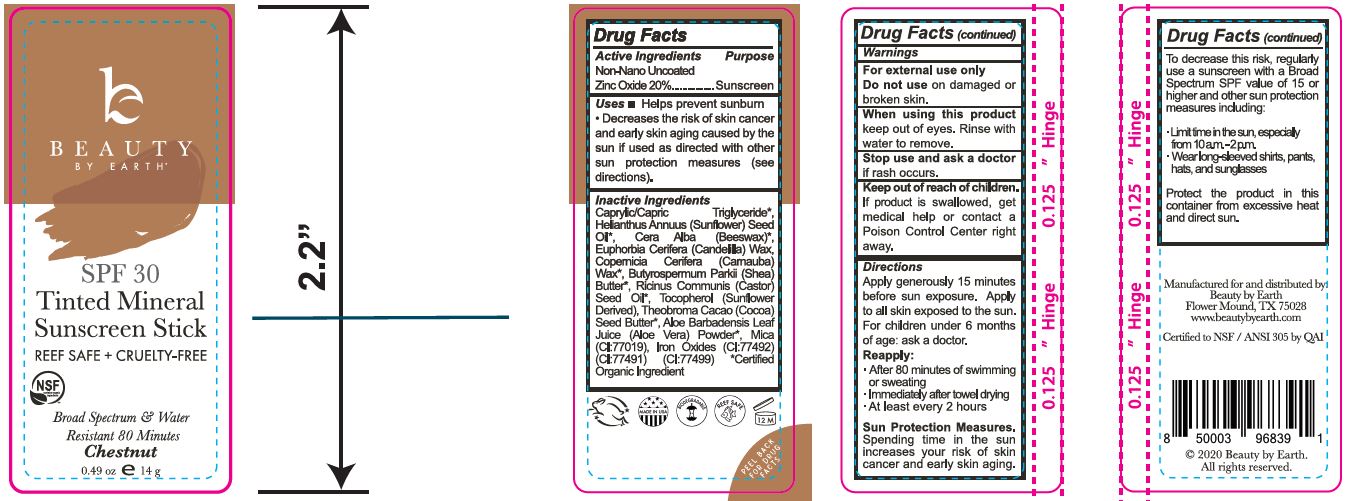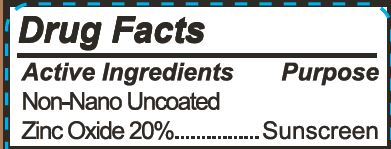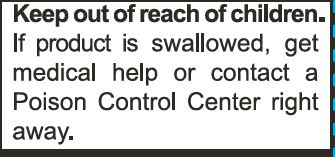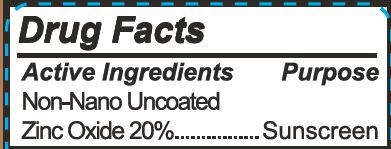 DRUG LABEL: Tinted Mineral Face Sunscreen Stick - Chestnut
NDC: 62932-224 | Form: STICK
Manufacturer: Private Label Select Ltd CO
Category: otc | Type: HUMAN OTC DRUG LABEL
Date: 20201228

ACTIVE INGREDIENTS: ZINC OXIDE 20 g/100 g
INACTIVE INGREDIENTS: FERROSOFERRIC OXIDE; CANDELILLA WAX; CASTOR OIL; FERRIC OXIDE RED; .GAMMA.-TOCOPHEROL; FERRIC OXYHYDROXIDE; .ALPHA.-TOCOPHEROL, D-; .BETA.-TOCOPHEROL; .DELTA.-TOCOPHEROL; MEDIUM-CHAIN TRIGLYCERIDES; SUNFLOWER OIL; WHITE WAX; MICA; CARNAUBA WAX; SHEA BUTTER; COCOA BUTTER; ALOE VERA LEAF

Beauty By Earth Tinted Mineral Face Sunscreen Stick - Chestnut